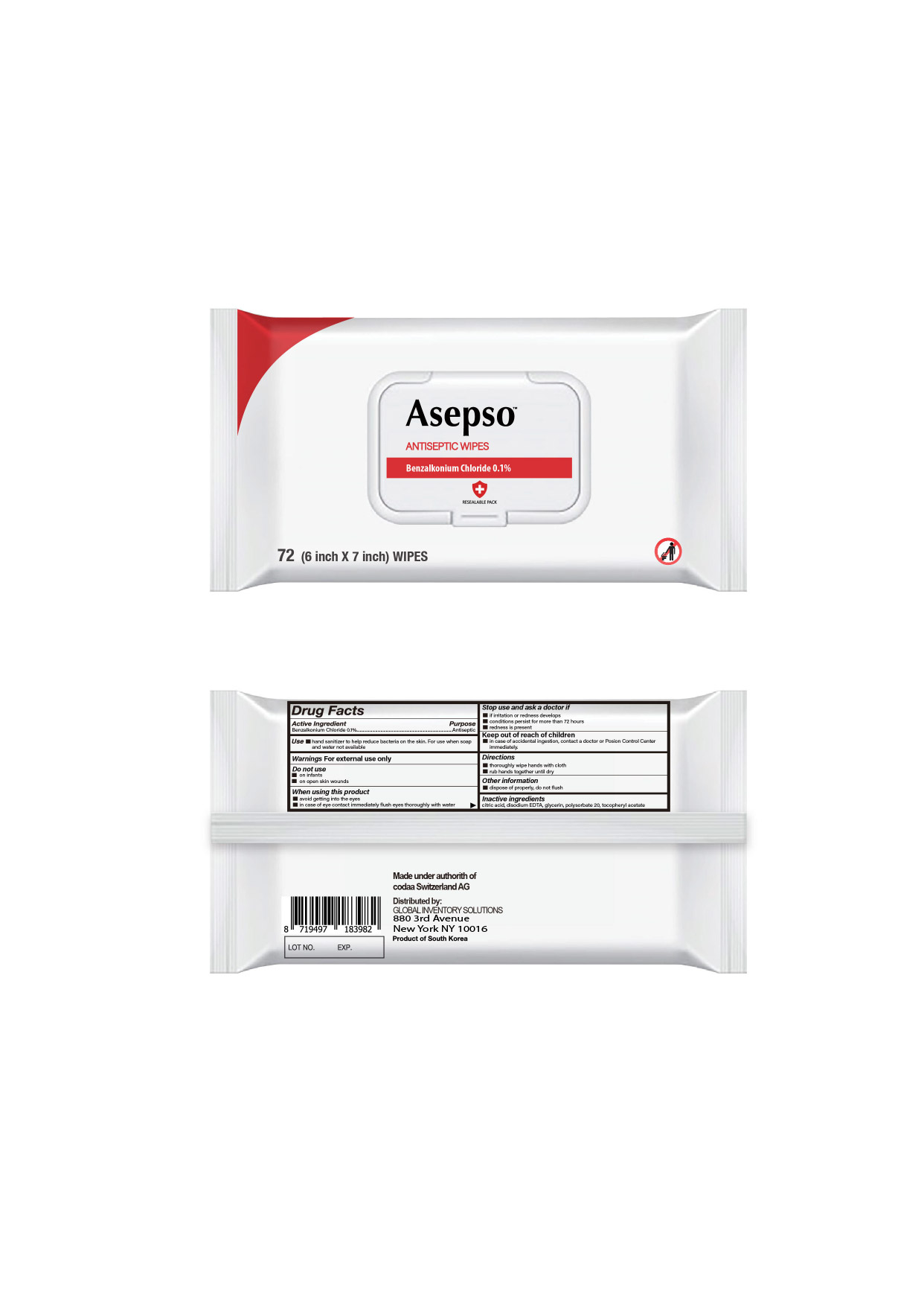 DRUG LABEL: Antiseptic Wipes
NDC: 79299-002 | Form: CLOTH
Manufacturer: GLOBAL INVENTORY SOLUTIONS CORP.
Category: otc | Type: HUMAN OTC DRUG LABEL
Date: 20220128

ACTIVE INGREDIENTS: BENZALKONIUM CHLORIDE 0.1 g/1 1
INACTIVE INGREDIENTS: POLYSORBATE 20; GLYCERIN; EDETATE SODIUM; .ALPHA.-TOCOPHEROL ACETATE; CITRIC ACID MONOHYDRATE

Asepso Wipes BKC0.1

Active ingredient

Benzalkonium chloride 0.1%

Purpose

Antiseptic

Use

■ hand sanitizer to help reduce bacteria on the skin. For use when soap and water not available

Warnings

For external use only

Do not use

■ on infants

■ on open skin wounds

When using this product

■ avoid getting into the eyes

■ in case of eye contact immediately flush eyes thoroughly with water

Stop use and ask a doctor if

■ irritation or redness develops

■ conditions persist for more than 72 hours

■ redness is present

Keep out of reach of children

■ in case of accidental ingestion, contact a doctor or Poison Control Center immediately.

Directions

■ thoroughly wipe hands with cloth

■ rub hands together until dry

Other information

■ dispose of properly, do not flush

Inactive ingredients

citric acid,disodium EDTA, glycerin, polysorbate 20, tocopheryl acetate